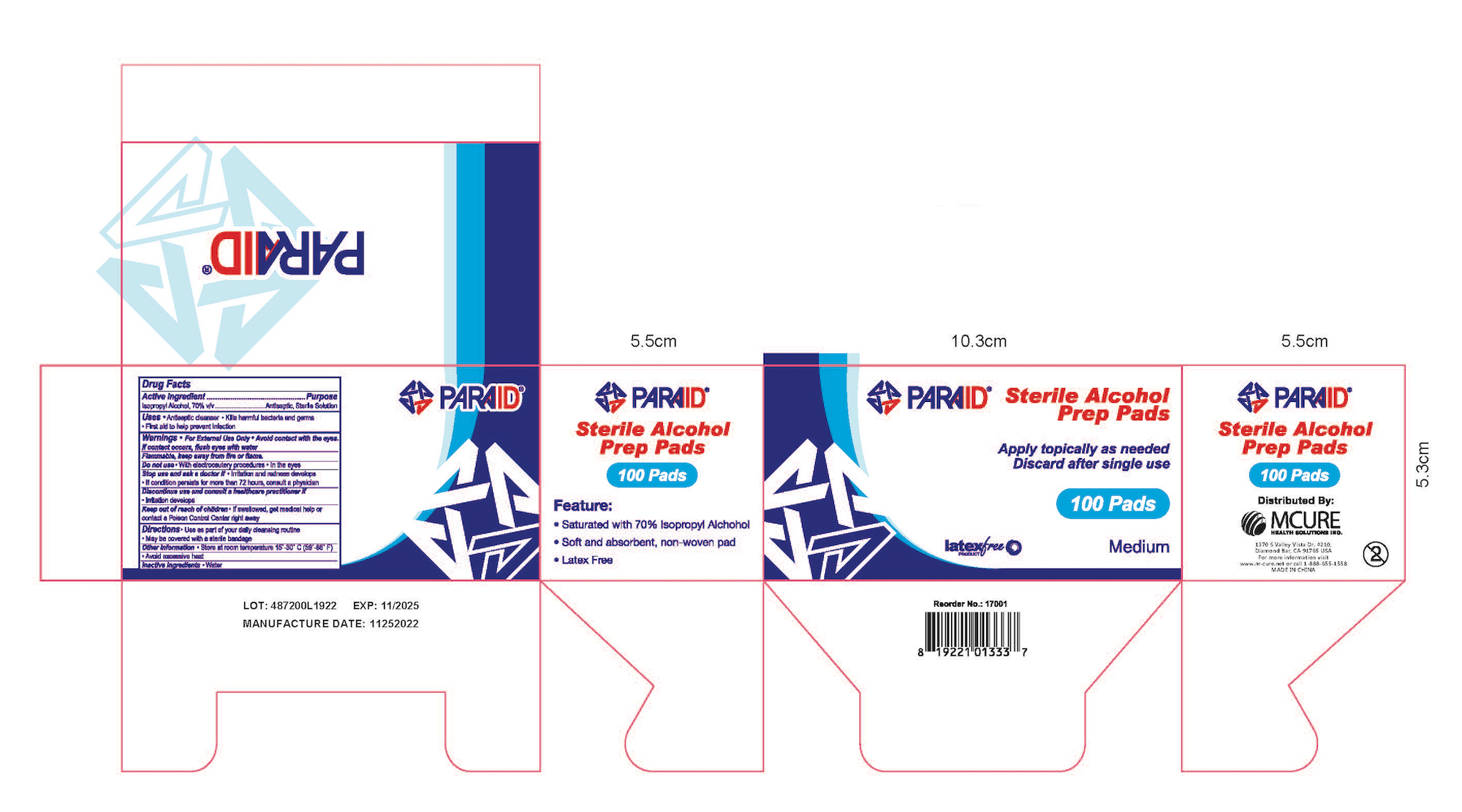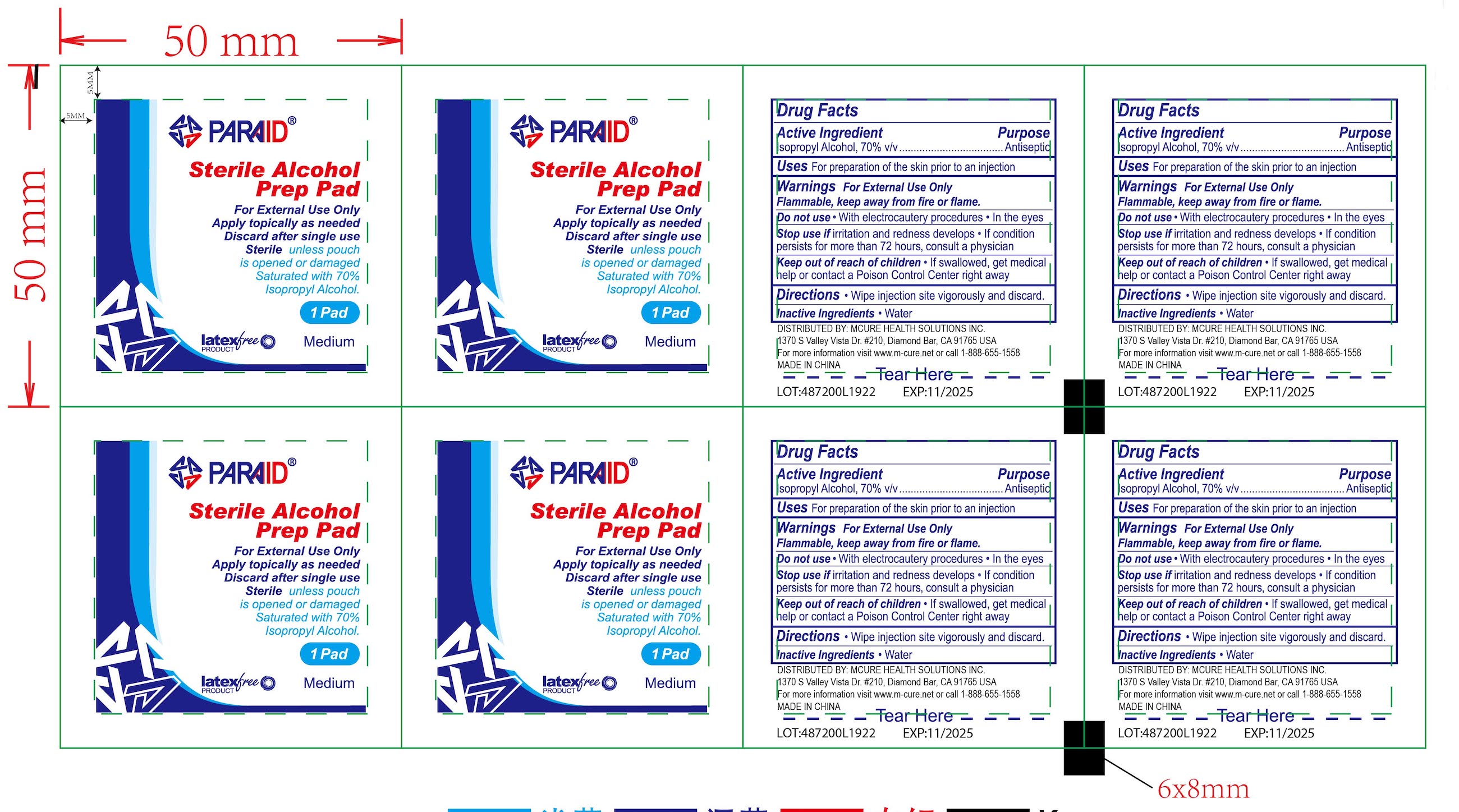 DRUG LABEL: isopropyl alcohol swab
NDC: 52486-051 | Form: SWAB
Manufacturer: Mcure Health Solutions Inc.
Category: otc | Type: HUMAN OTC DRUG LABEL
Date: 20230310

ACTIVE INGREDIENTS: ISOPROPYL ALCOHOL 70 g/100 g
INACTIVE INGREDIENTS: WATER

Active Ingredient

Isopropyl Alcohol, 70% v/v

Purpose

Antiseptic

Uses

For preparation of the skin prior to an injection

Directions

- Wipe injection site vigorously and discard

Warnings

For External Use Only

Flammable, keep away from fire or flame.

Do not use

- With electrocautery procedures
- In the eyes

Stop use

- if irritation and redness develops
- If condition persists for more than 72 hours, consult a physician

Inactive Ingredients

- Water

Keep out of reach of children

- If swallowed, get medical help or contact a Poison Control Center right away